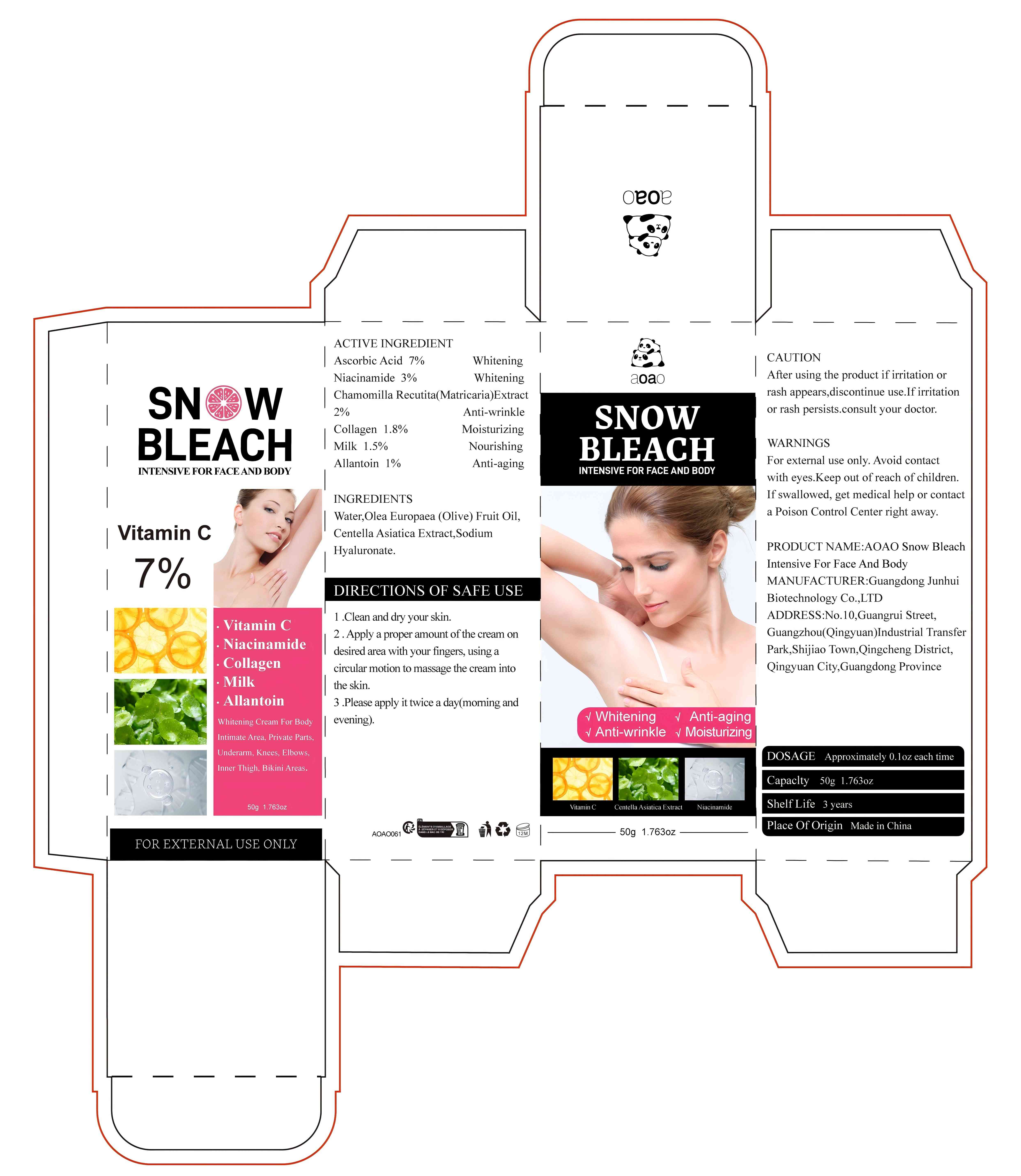 DRUG LABEL: AOAO Snow BIeach Intensive For Face And Body
NDC: 84509-025 | Form: CREAM
Manufacturer: Guangdong Junhui Biotechnology Co., LTD
Category: otc | Type: HUMAN OTC DRUG LABEL
Date: 20241018

ACTIVE INGREDIENTS: COW MILK 750 mg/50 g; ALLANTOIN 500 mg/50 g; ASCORBIC ACID 3500 mg/50 g; MATRICARIA CHAMOMILLA WHOLE 1000 mg/50 g; NIACINAMIDE 1500 mg/50 g; COLLAGEN, SOLUBLE, FISH SKIN 900 mg/50 g
INACTIVE INGREDIENTS: WATER; OLIVE OIL; CENTELLA ASIATICA TRITERPENOIDS; HYALURONATE SODIUM

Active Ingredients

Ascorbic Acid 7%

Niacinamide 3%
Chamomilla Recutita (Matricaria) Extract 2%
Collagen 1.80%
Milk 1.50%
Allantoin 1%

Purpose

Whitening
Anti-wrinkle
Moisturizing
Nourishing
Anti-aging

Uses

1 .Clean and dry your skin.
2 . Apply a proper amount of the cream on desired area with your fingers, using a circular motion to massage the cream into the skin.
3 .Please apply it twice a day(morning and evening)

Warnings

For external use only. Keep out ofreach of children.Avoid contact with eyes

Keep out of reach of children

If swallowed, get medical help or contact a Poison Control Center right away

CAUTION

After using the product if irritation or rash appears,discontinue use.If irritation or
rash persists.consult your doctor.

DOSAGE

Approximately 0.1 oz each time

MANUFACTURER

Guangdong Junhui Biotechnology Co., LTD

Product Name

AOAO Snow BIeach Intensive For Face And Body

Inactive Ingredients

Water,Olea Europaea (Olive) Fruit Oil,Centella Asiatica Extract,Sodium Hyaluronate

Address

No. 10, Guangrui Street, Guangzhou (Qingyuan) Industrial Transfer Park, Shijiao Town, Qingcheng District, Qingyuan City, Guangdong Province

Capacity

50g 1.763oz

Shelf Life

3 Years

Place of Origin

Made in China